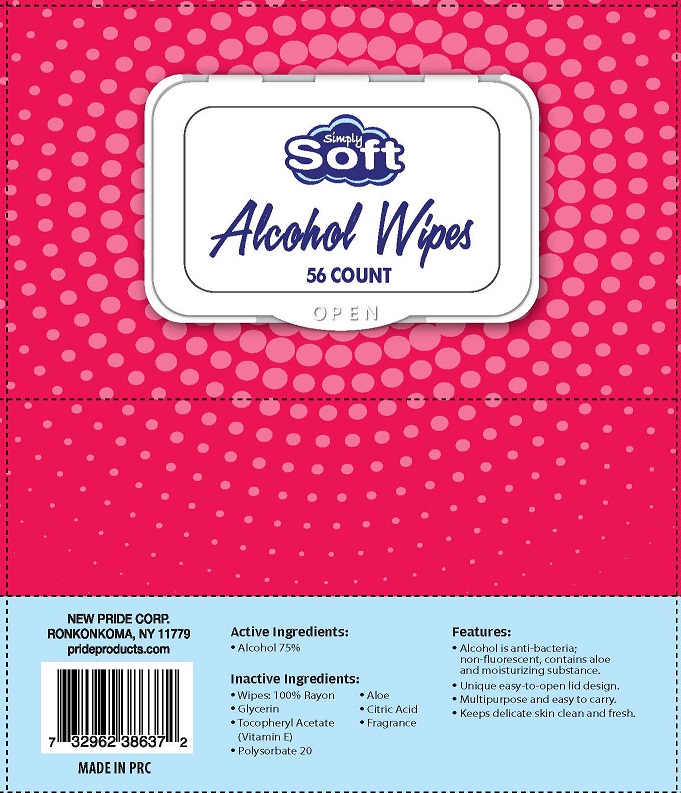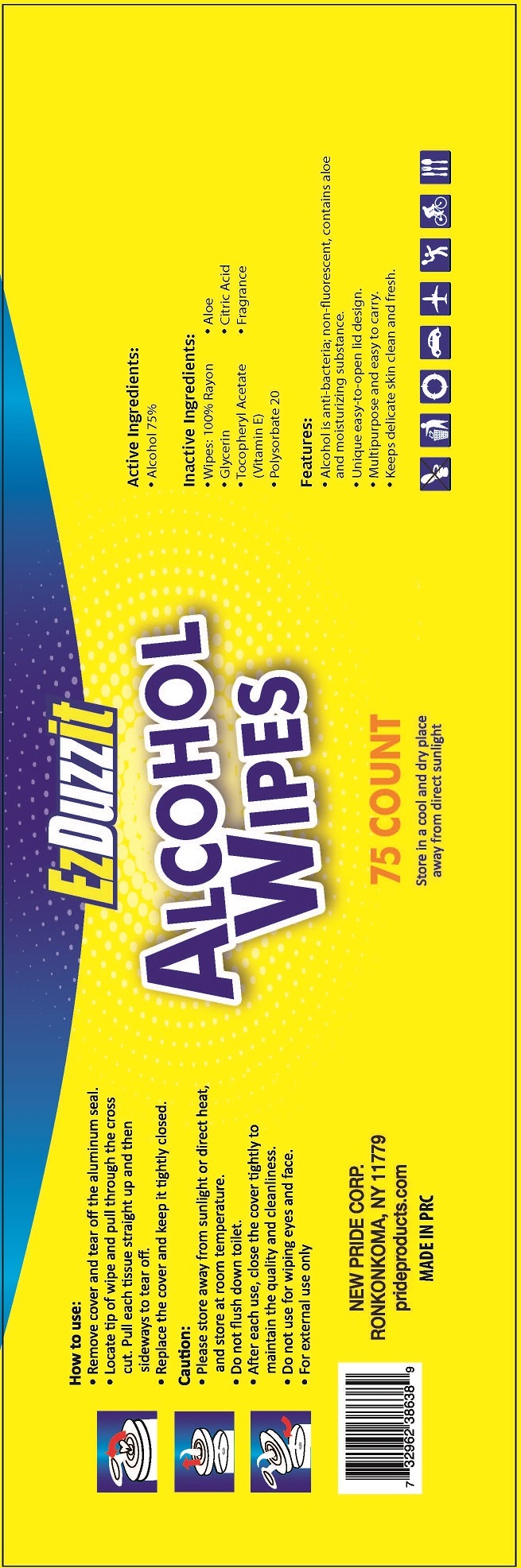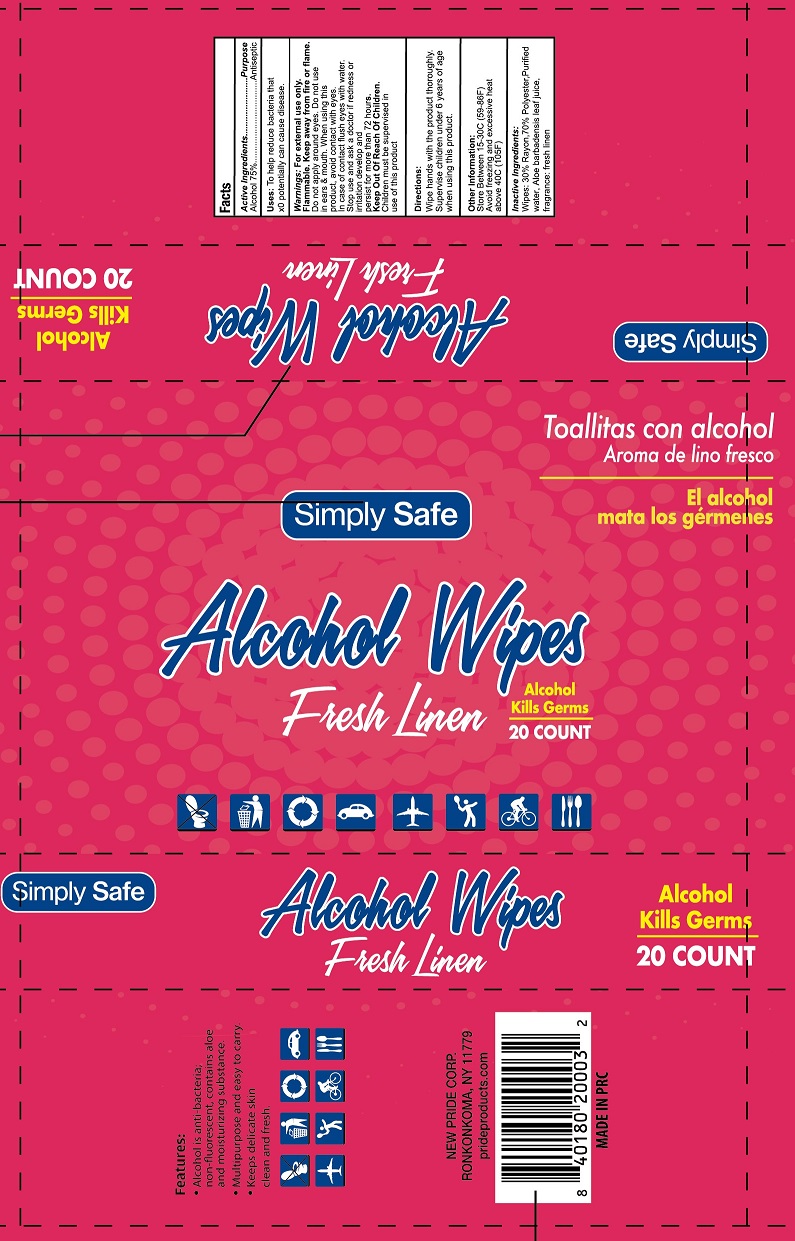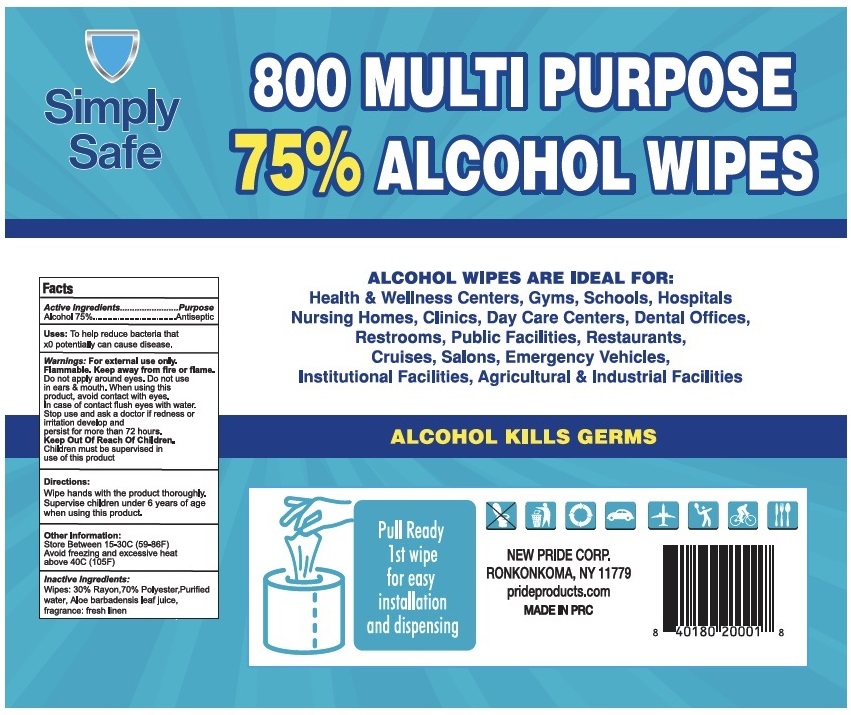 DRUG LABEL: ALCOHOL WIPES
NDC: 58037-101 | Form: SOLUTION
Manufacturer: Pride Products Corp.
Category: otc | Type: HUMAN OTC DRUG LABEL
Date: 20220113

ACTIVE INGREDIENTS: ALCOHOL 7.5 mL/1 1
INACTIVE INGREDIENTS: GLYCERIN; ALOE VERA LEAF; ANHYDROUS CITRIC ACID; POLYSORBATE 20; .ALPHA.-TOCOPHEROL ACETATE

PRIDE PRODUCTS - ALCOHOL WIPES (58037-101)

ACTIVE INGREDIENT

ALCOHOL 75%

PURPOSE

ANTI-BACTERIA

USES

KEEPS DELICATE SKIN CLEAN AND FRESH

WARNINGS

FOR EXTERNAL USE ONLY

Keep out of reach of children.

DIRECTIONS

UNIQUE EASY-TO-OPEN LID DESIGN.

MULTIPURPOSE AND EASY TO CARRY.

INACTIVE INGREDIENTS

- GLYCERIN
- ALOE
- TOCOPHERYL ACETATE (VITAMIN E)
- FRAGRANCE
- POLYSORBATE 20